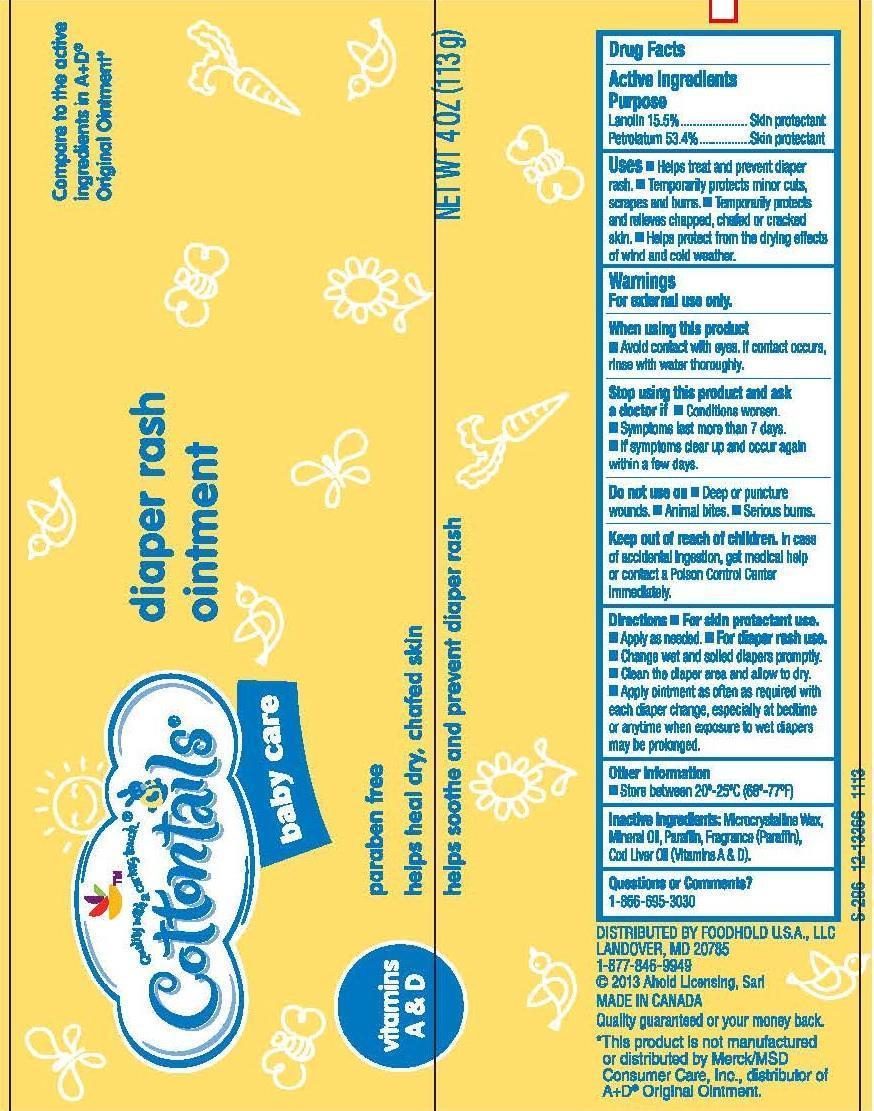 DRUG LABEL: COTTONTAILS
NDC: 41520-341 | Form: PASTE
Manufacturer: AMERICAN SALES COMPANY
Category: otc | Type: HUMAN OTC DRUG LABEL
Date: 20131217

ACTIVE INGREDIENTS: LANOLIN 155 mg/1 g; PETROLATUM 534 mg/1 g
INACTIVE INGREDIENTS: MICROCRYSTALLINE WAX; MINERAL OIL; PARAFFIN; COD LIVER OIL

DRUG FACTS

ACTIVE INGREDIENTS

LANOLIN 15.5%

PETROLATUM 53.4%

PURPOSE

SKIN PROTECTANT

USES

HELPS TREAT AND PREVENT DIAPER RASH. TEMPORARILY PROTECTS MINOR CUTS, SCRAPES AND BURNS. TEMPORARILY PROTECTS AND RELIEVES CHAPPED, CHAFED OR CRACKED SKIN. HELPS PROTECT FROM THE DRYING EFFECTS OF WIND AND COLD WEATHER

WARNINGS

FOR EXTERNAL USE ONLY

WHEN USING THIS PRODUCT

AVOID CONTACT WITH EYES. IF CONTACT OCCURS, RINSE WITH WATER THOROUGHLY

STOP USING THIS PRODUCT AND ASK A DOCTOR IF

CONDITION WORSENS. SYMPTOMS LAST MORE THAN 7 DAYS. IF SYMPTOMS CLEAR UP AND OCCUR AGAIN WITHIN A FEW DAYS

DO NOT USE ON

DEEP OR PUNCTURE WOUNDS. ANIMAL BITES. SERIOUS BURNS

KEEP OUT OF REACH OF CHILDREN

IN CASE OF ACCIDENTAL INGESTION, GET MEDICAL HELP OR CONTACT A POISON CONTROL CENTER IMMEDIATELY

DIRECTIONS

FOR SKIN PROTECTANT USE. APPLY AS NEEDED.

FOR DIAPER RASH USE. CHANGE WET AND SOILED DIAPERS PROMPTLY. CLEAN THE DIAPER AREA AND ALLOW TO DRY. APPLY OINTMENT AS OFTEN AS REQUIRED WITH EACH DIAPER CHANGE, ESPECIALLY AT BEDTIME OR ANYTIME WHEN EXPOSURE TO WET DIAPERS MAY BE PROLONGED

OTHER INFORMATION

STORE BETWEEN 20°-25°C (68°-77°F)

INACTIVE INGREDIENTS

MICROCRYSTALLINE WAX, MINERAL OIL, PARAFFIN, FRAGRANCE (PARFUM), COD LIVER OIL (VITAMINS A & D)

QUESTIONS OR COMMENTS?

1-866-695-3030